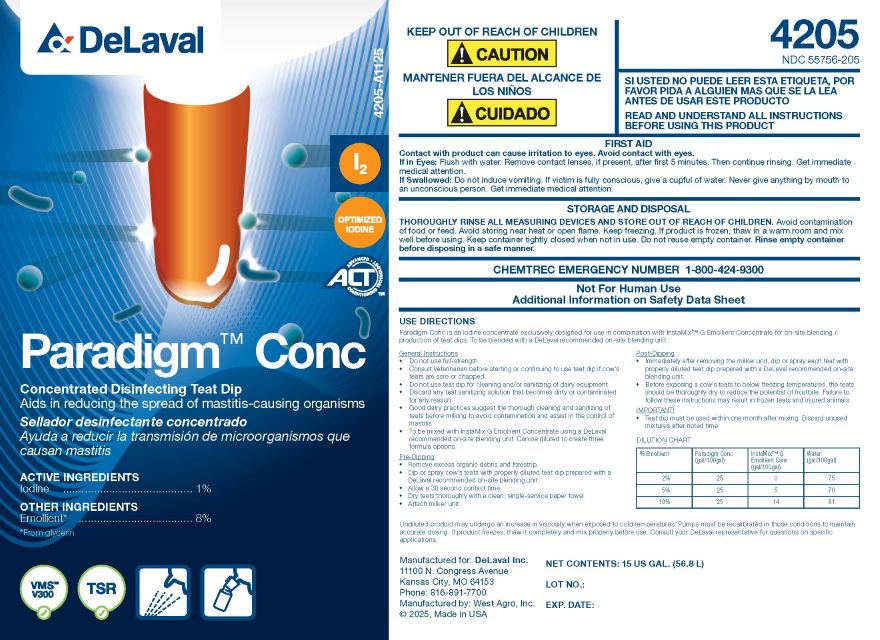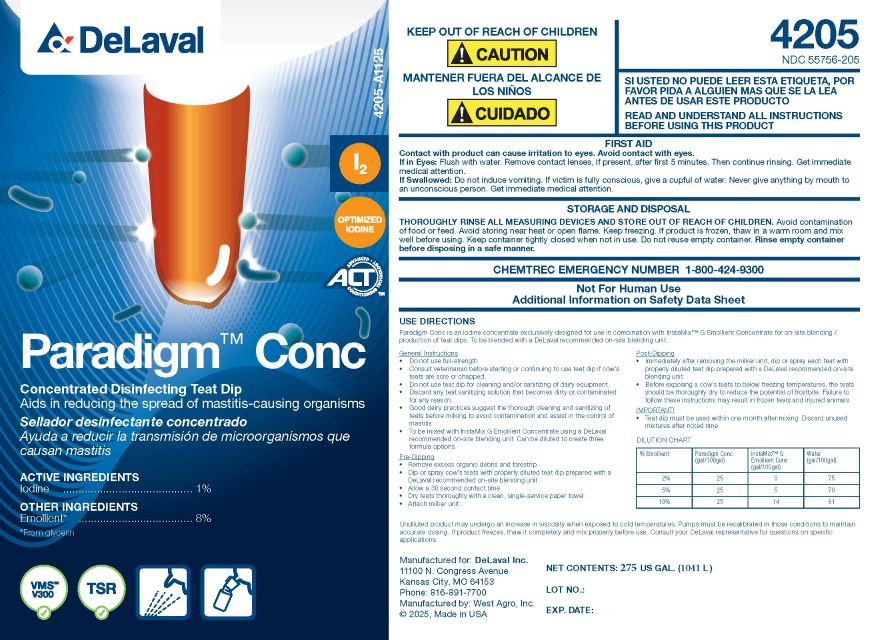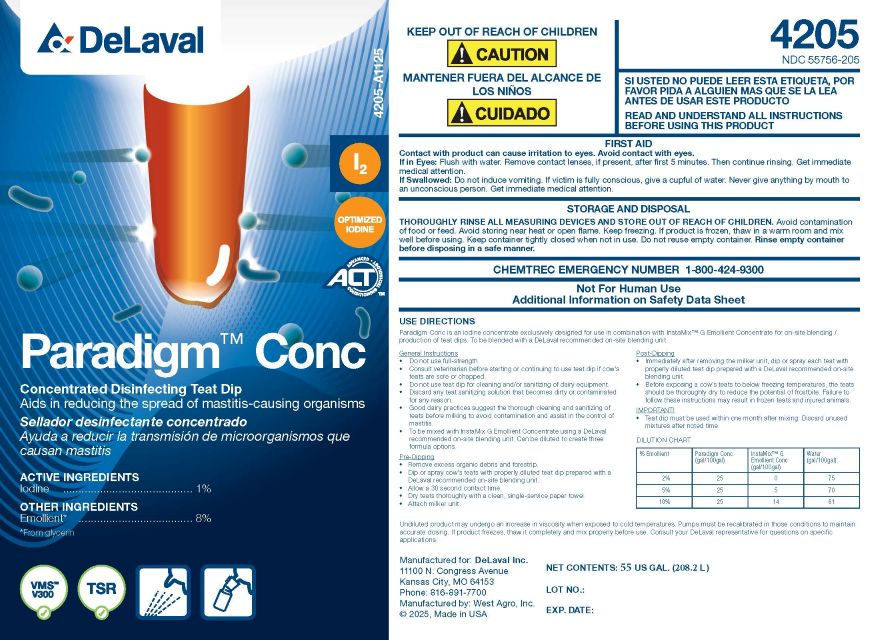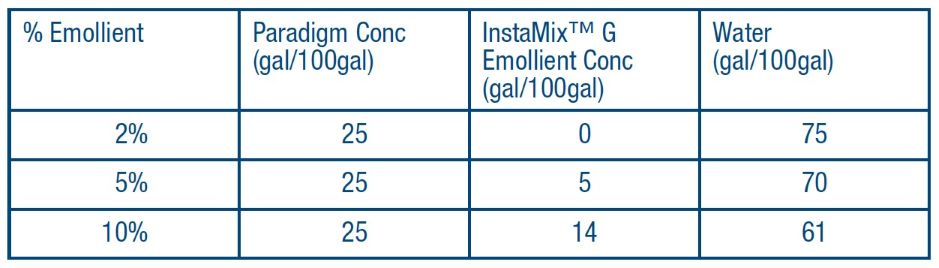 DRUG LABEL: Paradigm Conc
NDC: 55756-205 | Form: SOLUTION
Manufacturer: DeLaval
Category: animal | Type: OTC ANIMAL DRUG LABEL
Date: 20251220

ACTIVE INGREDIENTS: IODINE 10 g/1 L

DeLaval Della Barrier

Concentrated Disinfecting Teat Dip

Aids in reducing the spread of mastitis-causing organisms.

Sellador desinfactante concenrado

Ayuda a reducir la transmision de microorganismos que causan mastitis

ACTIVE INGREDIENTS:
Iodine ......................... 1.00%

OTHER INGREDIENTS

Emollient* .....................8%

*From glycerin

KEEP OUT OF REACH OF CHILDREN
! CAUTION

MANTENER FUERA DEL ALCANCE DE LOS NINOS
! CUIDADO

SI USTED NO PUEDE LEER ESTA ETIQUETA, POR FAVOR PIDA A ALGUIEN MAS QUE SE LA LEA ANTES DE USAR ESTE PRODUCTO

READ AND UNDERSTAND ALL INSTRUCTIONS BEFORE USING THIS PRODUCT

FIRST AID

Contact with product can cause irritation to eyes. Avoid contact with eyes.

If in eyes: Flush with water. Remove contact lenses, if present, after first 5 minutes. Then continue rinsing. Get immediate medical attention.

If Swallowed: Do not induce vomiting. If victim is conscious, give a cupful of water. Never give anything by mouth to an unconscious person. Get immediate medical attention.

STORAGE AND DISPOSAL
THOROUGHLY RINSE ALL MEASURING DEVICES AND STORE OUT OF REACH OF CHILDREN. Avoid contact with food or feed. Avoid storing near heat or open flame. Keep Freezing. If product has frozen, thaw in a warm room and mix well before using. Keep container tightly closed when not in use. Do not reuse empty container. Rinse empty container before disposing of in a safe manner.

CHEM-TREC EMERGENCY NUMBER 1-800-424-9300

Not For Human Use

Additional Information on Material Safety Data Sheet

USE DIRECTIONS

Paradigm Conc is an iodine concentrate exclusively designed for use in conbination with InstaMix G Emollent Concentrate for

on-site blending/production of teat dips. To be blended with a DeLaval recommended on-site bending unit.

General Instuctions.

- Do not use full-strength.
- Consult veterinarian before starting or continuing to use teat dip if cow's teats are score or chapped.
- Do not use teat dip for cleaning and/or sanitixing of dairy equipment.
- Discard any teat sanitizing solution that becomes dirty or contaminated for any reason.
- Good dairy practices suggest the thorough cleaning and sanitizing of teats before milkng to avoid contamination and assist in the control of mastitis.
- To be mixd with InstaMix G Emollient Concentrate using a DeLaval recommended on-site blending unit. Can be diluted to create three formula options.

Pre-Dipping

- Remove excess organic debris and forestrip
- Dip or spray cow's teats with properly diluted teat dip prepared with a DeLaval recommended on-site bledning unit.
- Allow a 30 second contact time.
- Attach milker unit.

Post-Dipping

- Immediately after removing the milker unit, dip or spray each teat with properly diluted teat dip prepared with a DeLaval recommended on-site blending unit.
- Before exposing a cow's teats to below freezing temperatures, the teats should be thoroughly dry to reduce the potential of frostbite. Failure to follow these instructions may result in frozen teats and injured animals.

IMPORTANT!

- Teat dip must be used within one month after mixing. Discard unused mixtures after noted time.

DILUTION CHART

Undiluted product may undergo an increase in viscosity when exposed to cold temperatures. Pumps must be recalibrated in those conditions to maintain accurate dosing. If product freezes, thaw it completely and mix properly before use. Consult your DeLaval representative for questions on specific applications.

PACKAGE LABEL

Manufactured for: DeLaval, Inc.
11100 N. Congress Avenue
Kansas City, MO 64153
Phone: 816-891-7700
Manufactured by: WestAgro, Inc.
©2025, Made in USA

NET CONTENTS:

LOT NO.:

EXP. DATE: